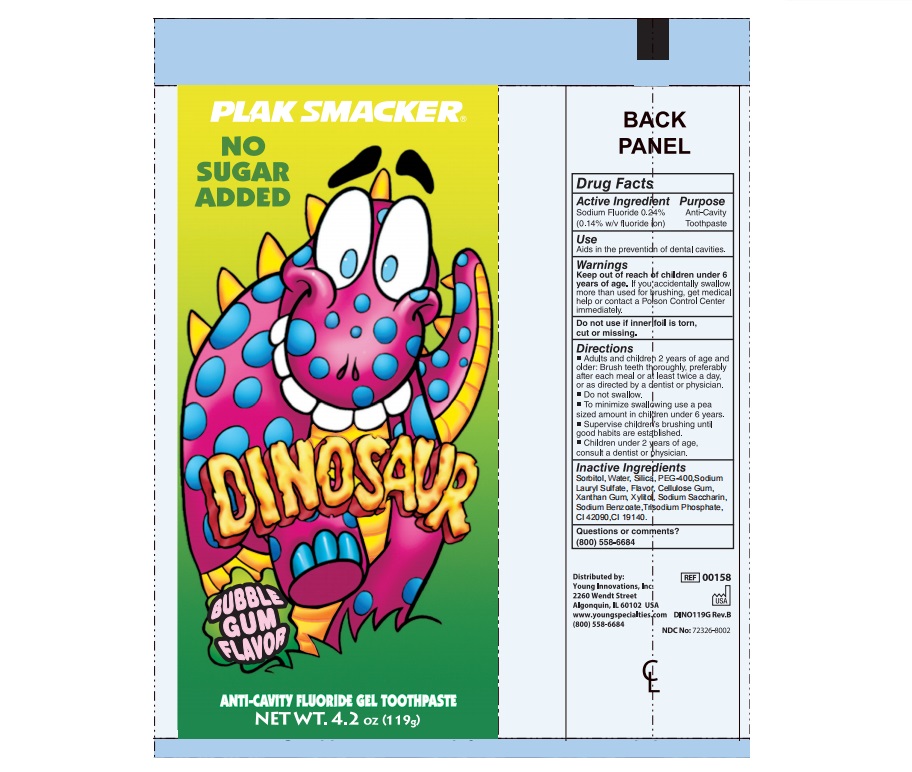 DRUG LABEL: DINOSAUR BUBBLE GUM FLAVOR ANTI-CAVITY FLUORIDE TOOTH
NDC: 70766-016 | Form: PASTE, DENTIFRICE
Manufacturer: Yangzhou SION Commodity Co.,Ltd
Category: otc | Type: HUMAN OTC DRUG LABEL
Date: 20240721

ACTIVE INGREDIENTS: SODIUM FLUORIDE 0.14 g/100 g
INACTIVE INGREDIENTS: WATER; SORBITOL; HYDRATED SILICA; SODIUM LAURYL SULFATE; CALCIUM CARBONATE; POLYETHYLENE GLYCOL 400; SACCHARIN SODIUM; SODIUM BENZOATE; XYLITOL; CARBOXYMETHYLCELLULOSE SODIUM; FD&C BLUE NO. 1; FD&C YELLOW NO. 5; SODIUM PHOSPHATE

70766-016 Dinosuair anticavity gel tooth paste

Active ingredients

SODIUM FLUORIDE 0.24%(0.14 w/v Fluoride ion)

<text xmlns="urn:hl7-org:v3"> <paragraph>SODIUM FLUORIDE 0.24%(0.11 w/v Fluoride ion)</paragraph> <paragraph/>&lt;text xmlns="urn:hl7-org:v3"> &lt;paragraph>SODIUM FLUORIDE 0.24%(0.11 w/v Fluoride ion)&lt;/paragraph> &lt;paragraph/>&amp;lt;text xmlns="urn:hl7-org:v3"> &amp;lt;paragraph>SODIUM FLUORIDE 0.24%(0.10 w/v Fluoride ion)&amp;lt;/paragraph> &amp;lt;paragraph/>&amp;amp;lt;text xmlns="urn:hl7-org:v3"> &amp;amp;lt;paragraph>SODIUM FLUORIDE 0.24%(0.10 w/v Fluoride ion)&amp;amp;lt;/paragraph> &amp;amp;lt;paragraph/>&amp;amp;amp;lt;text xmlns="urn:hl7-org:v3"> &amp;amp;amp;lt;paragraph>SODIUM FLUORIDE 0.24%(0.10 w/v Fluoride ion)&amp;amp;amp;lt;/paragraph> &amp;amp;amp;lt;paragraph/> &amp;amp;amp;lt;/text>&amp;amp;lt;/text>&amp;lt;/text>&lt;/text></text>

Purpose

Anticavity

Uses

Aids in the prevention of dental cavities.

Warnings

Keep out of the reach of children under 6 years of age. If you accidently swallow more than used for brushing, get medical help or contact a Poison Control Center immediately.

Keep out of reach of children.

Directions

- Adults and children 2 years of age and older: Brush teeth thoroughly, preferrably after each meal or at least twice a day, or as directed by a dentist or a doctor.
- Do not swallow
- To minimize swallowing, use a pea sized amount in children under 6 years
- Supervise children brushing untill good habits are established
- Children under 2 years of age: Consult a dentist or physician.

INACTIVE INGREDIENT

Sorbitol,, Water, Silica, PEG-400, Sodium Lauryl Sulfate, Flavor, Cellulose Gum, Xanthan Gum, Xylitor, Sodium Sacharine, Sodium Benzoate, Sodium Phosphate, CI 42090, CI 19140